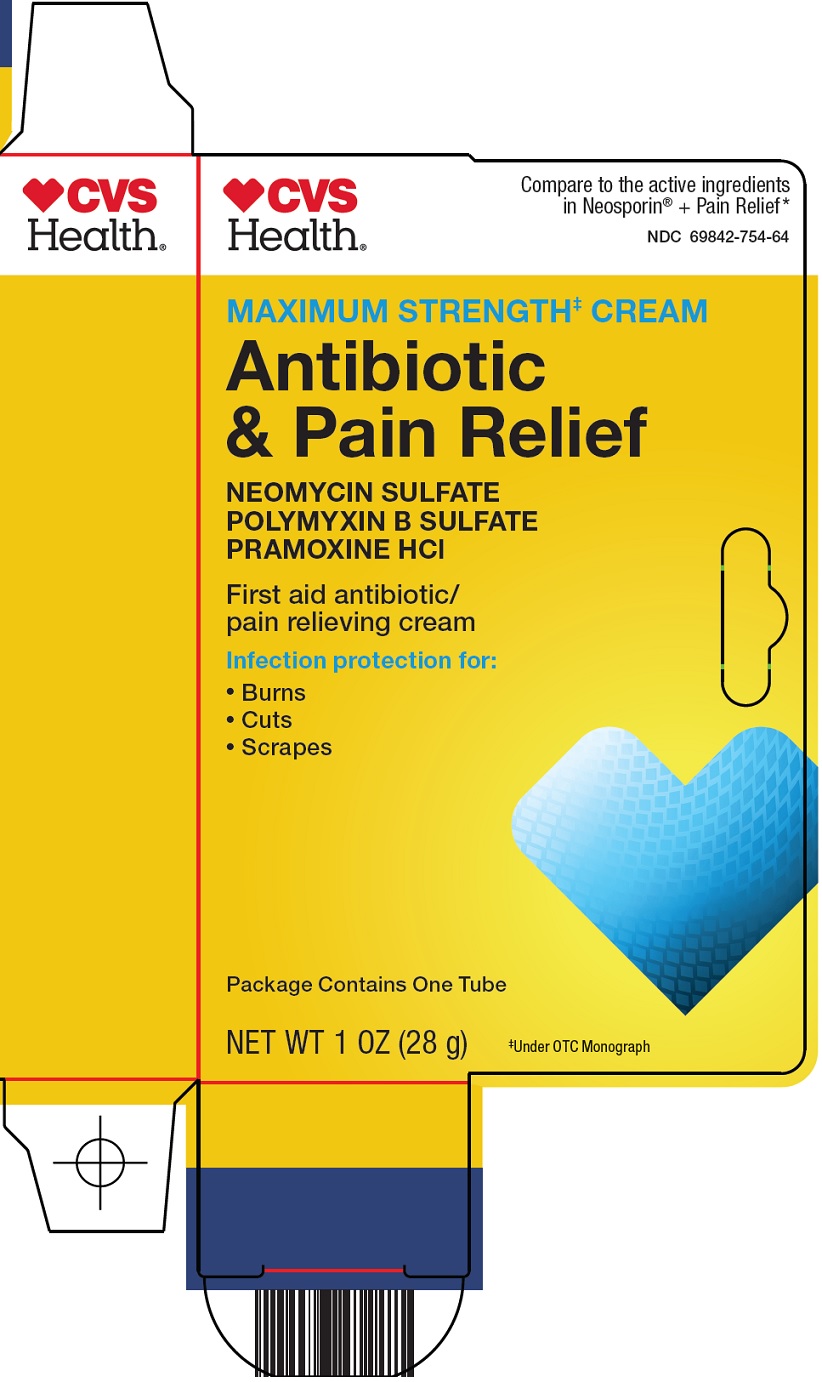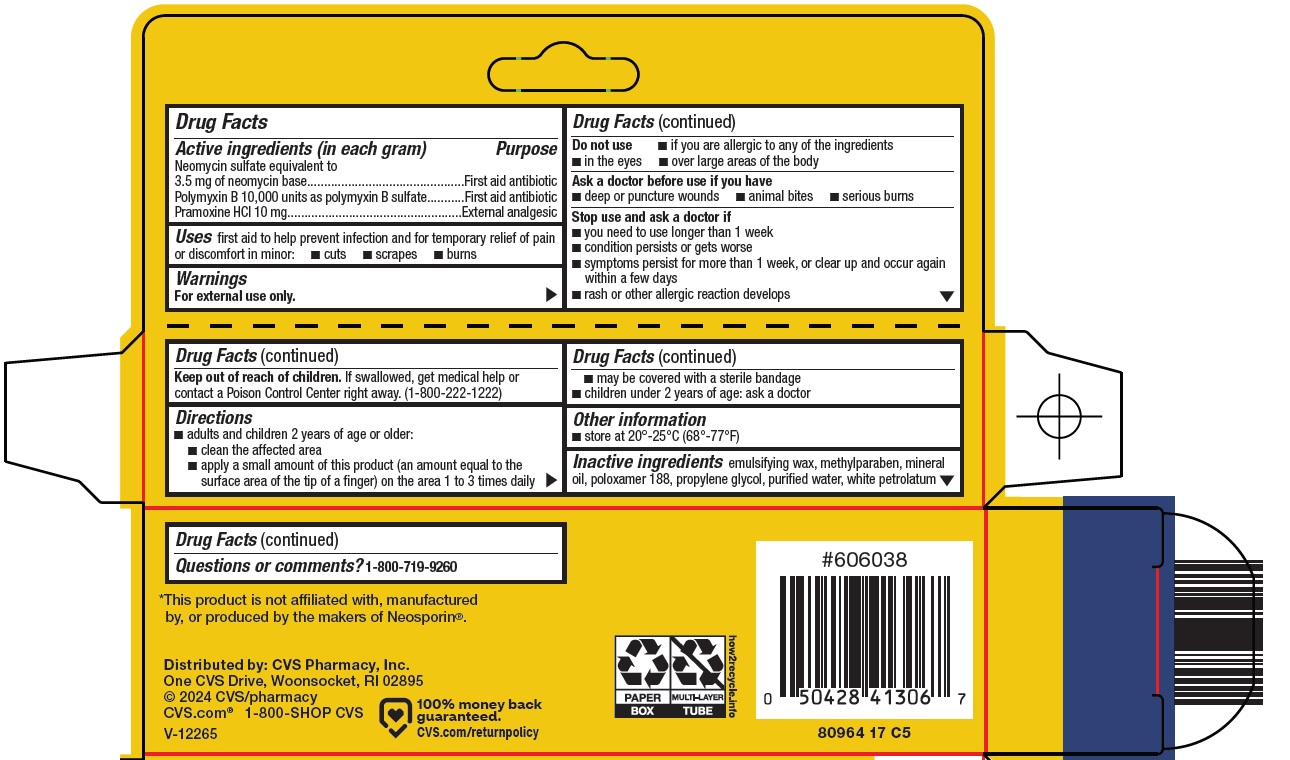 DRUG LABEL: Antibiotic and Pain Relief
NDC: 69842-754 | Form: CREAM
Manufacturer: CVS Pharmacy
Category: otc | Type: HUMAN OTC DRUG LABEL
Date: 20241014

ACTIVE INGREDIENTS: NEOMYCIN SULFATE 3.5 mg/1 g; PRAMOXINE HYDROCHLORIDE 10 mg/1 g; POLYMYXIN B SULFATE 10000 [USP'U]/1 g
INACTIVE INGREDIENTS: METHYLPARABEN; MINERAL OIL; POLOXAMER 188; PROPYLENE GLYCOL; WATER; PETROLATUM

CVS Pharmacy, Inc. Antibiotic and Pain Relief Drug Facts

Active ingredient (in each gram)

Neomycin sulfate equivalent to 3.5 mg of neomycin base

Polymyxin B 10,000 units as polymyxin B sulfate

Pramoxine HCl 10 mg

Purpose

First aid antibiotic

External analgesic

Uses

first aid to help prevent infection and for temporary relief of pain or discomfort in minor:

- cuts
- scrapes
- burns

Warnings

For external use only.

Do not use

- if you are allergic to any of the ingredients
- in the eyes
- over large areas of the body

Ask a doctor before use if you have

- deep or puncture wounds
- animal bites
- serious burns

Stop use and ask a doctor if

- you need to use longer than 1 week
- condition persists or gets worse
- symptoms persist for more than 1 week, or clear up and occur again within a few days
- rash or other allergic reaction develops

Keep out of reach of children.

If swallowed, get medical help or contact a Poison Control Center right away. (1-800-222-1222)

Directions

- adults and children 2 years of age or older:
- clean the affected area
- apply a small amount of this product (an amount equal to the surface area of the tip of a finger) on the area 1 to 3 times daily
- may be covered with a sterile bandage
- children under 2 years of age: ask a doctor

Other information

- store at 20o-25oC (68o-77oF)

Inactive ingredients

emulsifying wax, methylparaben, mineral oil, poloxamer 188, propylene glycol, purified water, white petrolatum

Questions or comments?

1-800-719-9260

Principal Display Panel

CVS Health®

Compare to the active ingredients in Neosporin® + Pain Relief

MAXIMUM STRENGTH‡ CREAM

Antibiotic & Pain Relief

NEOMYCIN SULFATE

POLYMYXIN B SULFATE

PRAMOXINE HCl

First aid antibiotic/pain relieving cream

Infection protection for:

• Burns

• Cuts

• Scrapes

Package Contains One Tube

NET WT 1 OZ (28 g)

‡Under OTC Monograph